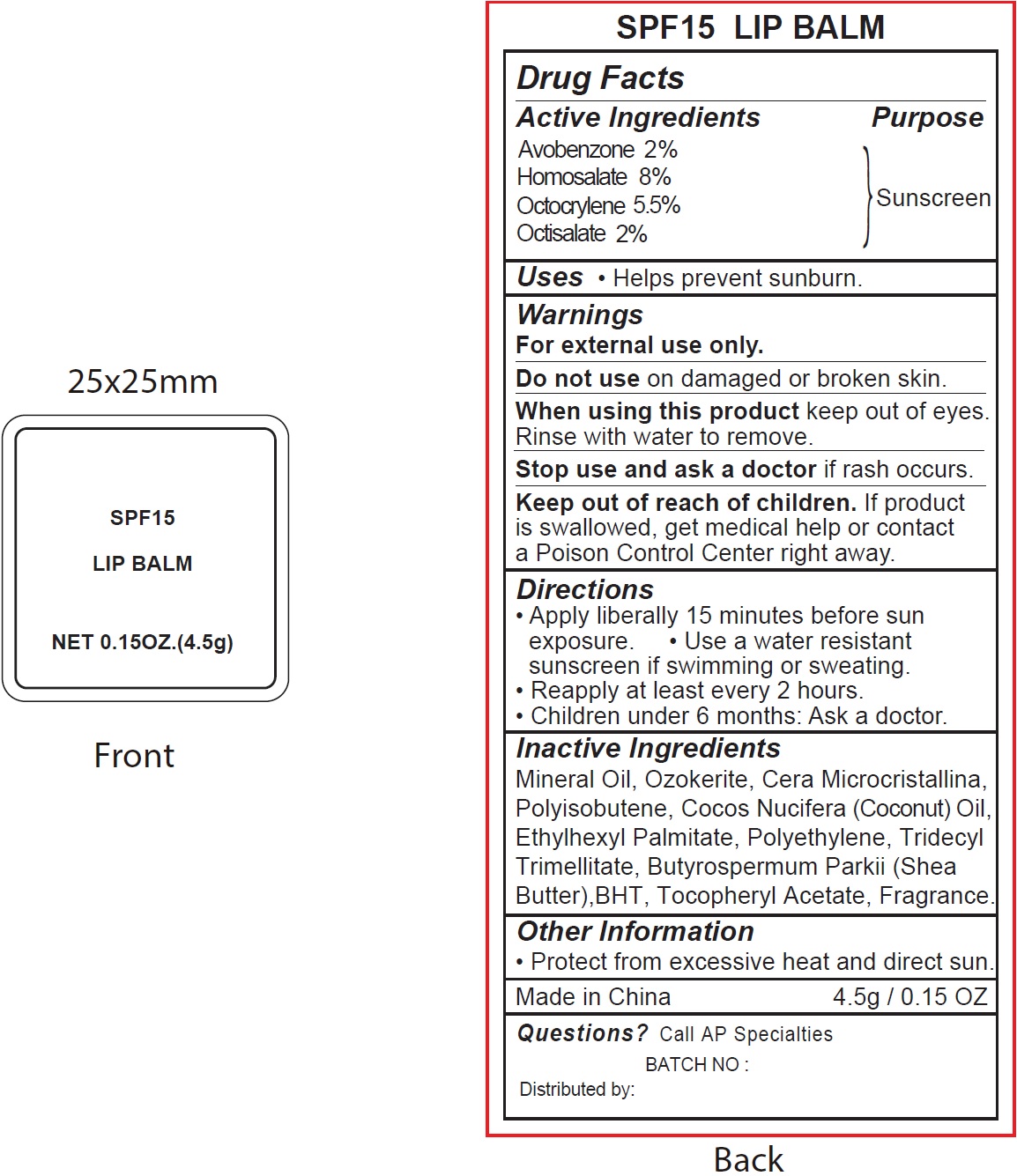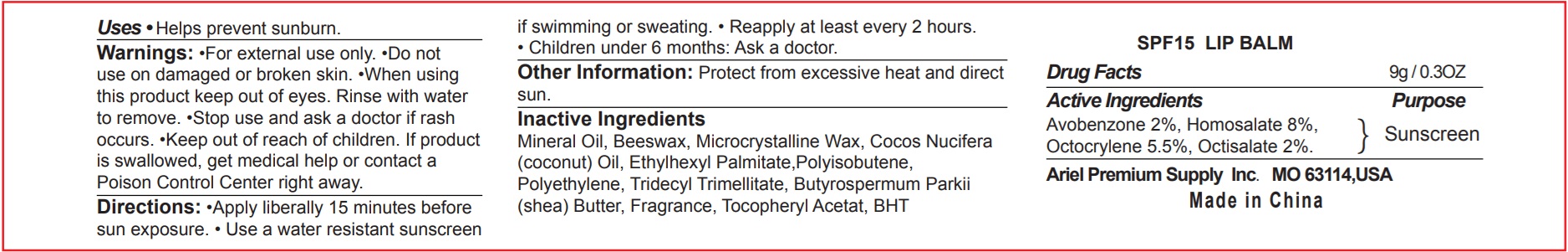 DRUG LABEL: SPF15
NDC: 70412-316 | Form: LIPSTICK
Manufacturer: Zhejiang Ayan Biotech Co.,Ltd.
Category: otc | Type: HUMAN OTC DRUG LABEL
Date: 20240826

ACTIVE INGREDIENTS: AVOBENZONE 20 mg/1 g; HOMOSALATE 80 mg/1 g; OCTOCRYLENE 55 mg/1 g; OCTISALATE 20 mg/1 g
INACTIVE INGREDIENTS: MINERAL OIL; CERESIN; COCONUT OIL; ETHYLHEXYL PALMITATE; HIGH DENSITY POLYETHYLENE; TRIDECYL TRIMELLITATE; SHEA BUTTER; BUTYLATED HYDROXYTOLUENE; .ALPHA.-TOCOPHEROL ACETATE

SPF15 Lip Balm

Active Ingredients

Avobenzone 2% Octocrylene 8% Octisalate 5.5% Homosalate 2%

Purpose

Sunscreen

Uses

- Helps prevent sunburn.

Warnings

For external use only.

Do not use

on damaged or broken skin.

When using this product

keep out of eyes. Rinse with water to remove.

Stop use and ask a doctor

if reash occurs.

Keep out of reach of children.

If product is swallowed, get medical help or contact a Poison Control right away.

Directions

- Apply liberally 15 minutes before sun exposure.
- Usa a water resistant sunscreen if swimming or sweating.
- Reapply at least every 2 hours.
- Children under 6 months: Ask a doctor.

Inactive Ingredients

Mineral Oil, Ozokerite, Cera Microcristallina, Polyisobutene, Cocos Nucifera (Coconut) Oil, Ethylhexyl Palmitate, Polyethylene, Tridencyl Trimellitate, Butyrospermum Parkii (Shea Butter), BHT, Tocopheryl Acetate, Fragrance.

Other Information

- Protect from excessive heat and direct sun.

Questions?

Call AP Specialties

BATCH NO:

Distributed by: